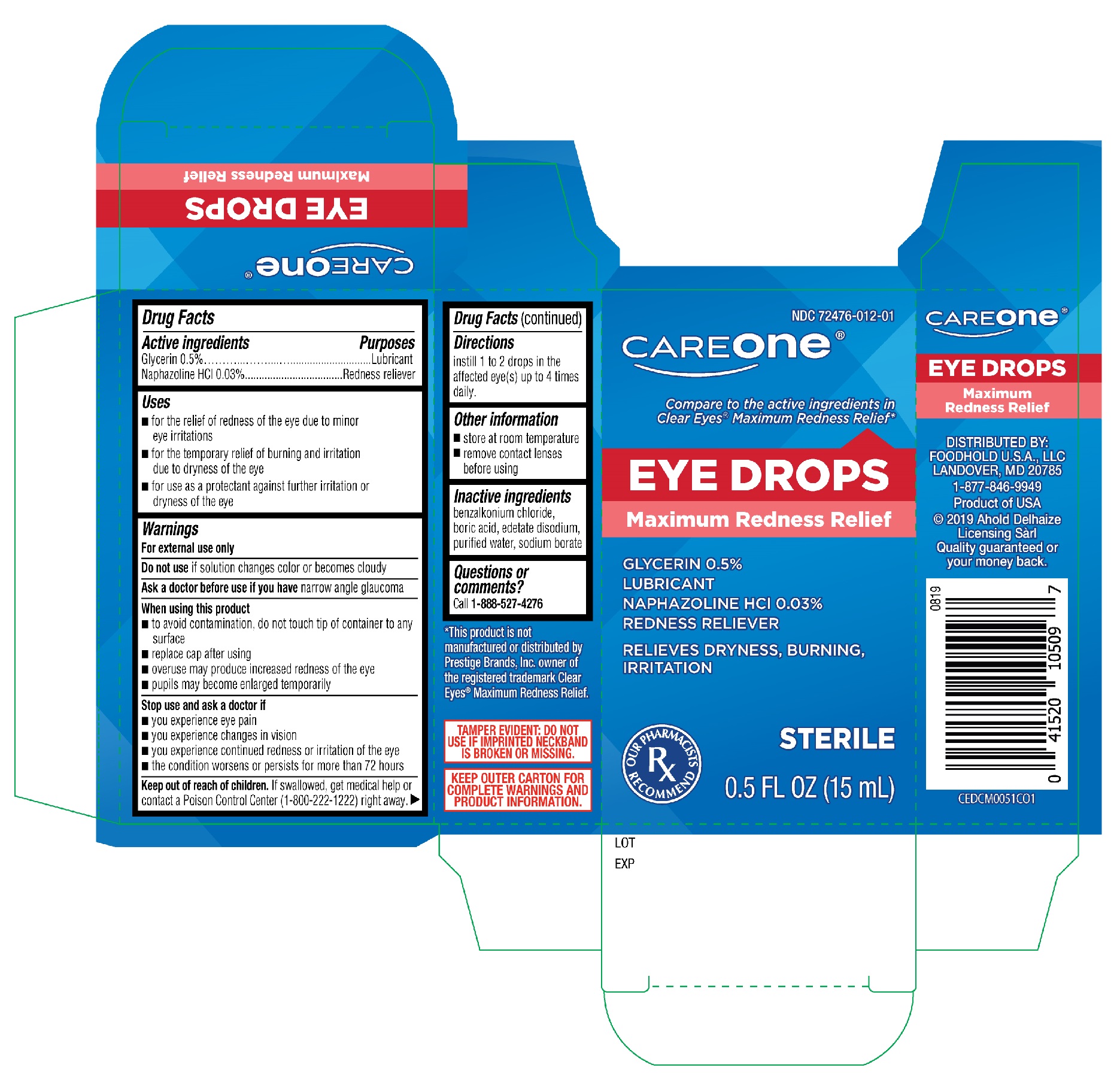 DRUG LABEL: CareOne Maximum Redness Relief Eye Drops
NDC: 72476-012 | Form: SOLUTION/ DROPS
Manufacturer: Retail Business Services, LLC
Category: otc | Type: HUMAN OTC DRUG LABEL
Date: 20251230

ACTIVE INGREDIENTS: GLYCERIN 0.5 g/100 mL; NAPHAZOLINE HYDROCHLORIDE 0.03 g/100 mL
INACTIVE INGREDIENTS: BENZALKONIUM CHLORIDE; BORIC ACID; SODIUM BORATE; EDETATE DISODIUM; WATER

CareOne Maximum Redness Relief Eye Drops (PLD)

Active ingredients

Glycerin 0.5%

Naphazoline HCI 0.03%

Purposes

Lubricant

Redness reliever

Uses

- for the relief of redness of the eye due to minor eye irriatations
- for the temporary relief of burning and irritation due to dryness of the eye
- for use as a protectant against further irritation or dryness of the eye

Warnings

For external use only

Do not use

if solution changes color or becomes cloudy

Ask a doctor before use if you have

narrow angle glaucoma

When using this product

- to avoid contamination, do not touch tip of container to any surface
- replace cap after using
- overuse may produce increased redness of the eye
- pupils may become enlarged temporarily

Stop use and ask a doctor if

- you experience eye pain
- you experience changes in vision
- you experience continued redness or irritation of the eye
- the condition worsens or persists for more than 72 hours

Keep out of reach of children.

If swallowed, get medical help or contact a Poison Control Center (1-800-222-1222) right away.

Directions

instill 1 or 2 drops in the affected eye(s) up to 4 times daily.

Other information

- store at room temperature
- remove contact lenses before using

Inactive ingredients

benzalkonium chloride, boric acid, edetate disodium, purified water, sodium borate

Questions or comments?

Call 1-888-527-4276